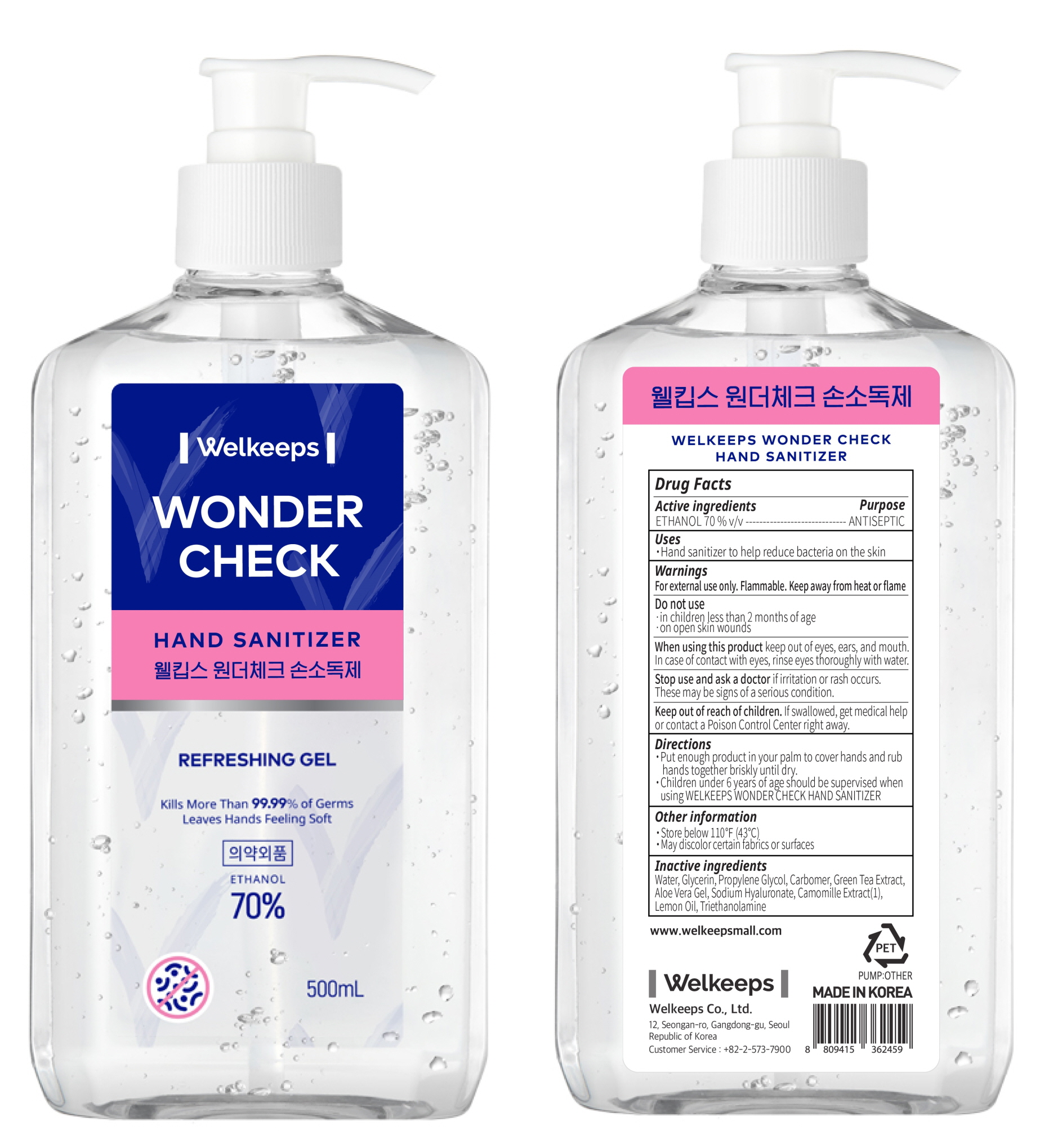 DRUG LABEL: WELKEEPS WONDER CHECK HAND SANITIZER
NDC: 78570-010 | Form: GEL
Manufacturer: Welkeeps Co.,Ltd.
Category: otc | Type: HUMAN OTC DRUG LABEL
Date: 20200604

ACTIVE INGREDIENTS: Alcohol 350 mL/500 mL
INACTIVE INGREDIENTS: Water; Glycerin; Propylene Glycol; CARBOMER HOMOPOLYMER, UNSPECIFIED TYPE; GREEN TEA LEAF; ALOE VERA LEAF; HYALURONATE SODIUM; CHAMOMILE; Lemon Oil; TROLAMINE

ACTIVE INGREDIENT

ETHANOL 70 % v/v

INACTIVE INGREDIENT

Water, Glycerin, Propylene Glycol, Carbomer, Green Tea Extract, Aloe Vera Gel, Sodium Hyaluronate, Camomille Extract(1), Lemon Oil, Triethanolamine

PURPOSE

ANTISEPTIC

WARNINGS

For external use only. Flammable. Keep away from heat or flame
--------------------------------------------------------------------------------------------------------
Do not use
• in children less than 2 months of age
• on open skin wounds
--------------------------------------------------------------------------------------------------------
When using this product keep out of eyes, ears, and mouth. In case of contact with eyes, rinse eyes thoroughly with water.
--------------------------------------------------------------------------------------------------------
Stop use and ask a doctor if irritation or rash occurs. These may be signs of a serious condition.

KEEP OUT OF REACH OF CHILDREN

If swallowed, get medical help or contact a Poison Control Center right away.

Uses

Hand sanitizer to help reduce bacteria on the skin.

Directions

• Put enough product in your palm to cover hands and rub hands together briskly until dry.
• Children under 6 years of age should be supervised when using WELKEEPS WONDER CHECK HAND SANITIZER

Other Information

• Store below 110℉ (43℃)
• May discolor certain fabrics or surfaces